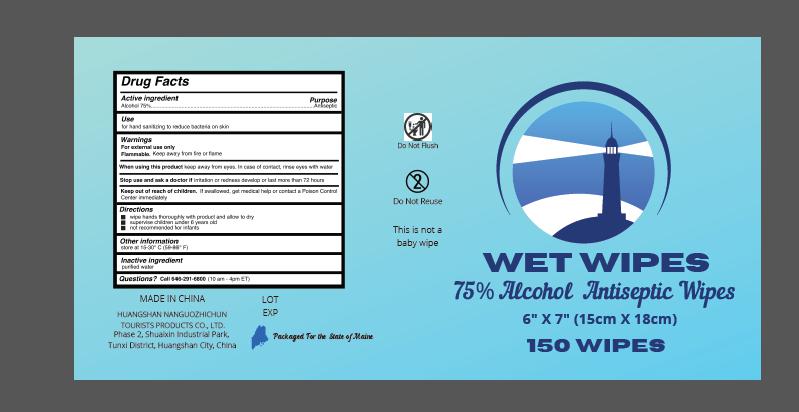 DRUG LABEL: WET WIPES
NDC: 78736-003 | Form: CLOTH
Manufacturer: HUANGSHAN NANGUOZHICHUN TOURISTS PRODUCTS CO., LTD.
Category: otc | Type: HUMAN OTC DRUG LABEL
Date: 20200810

ACTIVE INGREDIENTS: ALCOHOL 75 g/100 g
INACTIVE INGREDIENTS: WATER

WET WIPES

Active Ingredient(s)

Alcohol 75%

Purpose

Antiseptic

Use

For hand sanitizer to reduce bacteria on the skin

Warnings

For external use only.

Flammable, keep product away from fire or flame.

When using this product keep away from eyes.In case of contact,rinse eyes with water.

Stop use and ask a doctor if irritation or rash develops and continues for more than 72 hours.

Keep out of reach of children. If swallowed, get medical help or contact a Poison Control Center right away.

Directions

- Wet hands thoroughly with product and allow to dry
- Supervise children under 6 years old
- Not recommended for repeats

Inactive ingredients

Purified water

Other informations

Store at 15-30℃

Package Label - Principal Display Panel

150 PCS IN 1 PAIL NDC: 78736-003-01